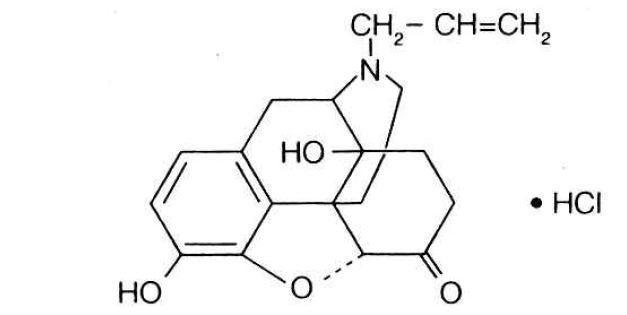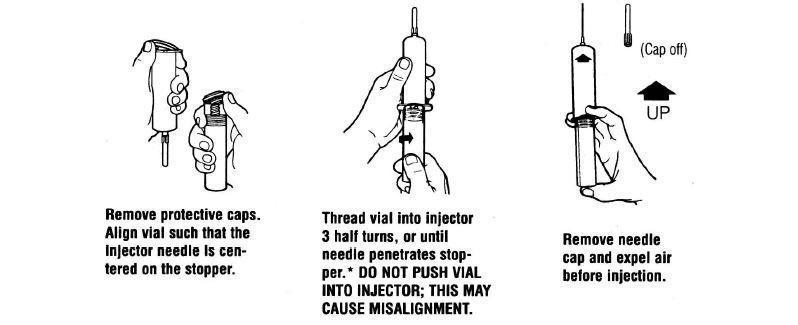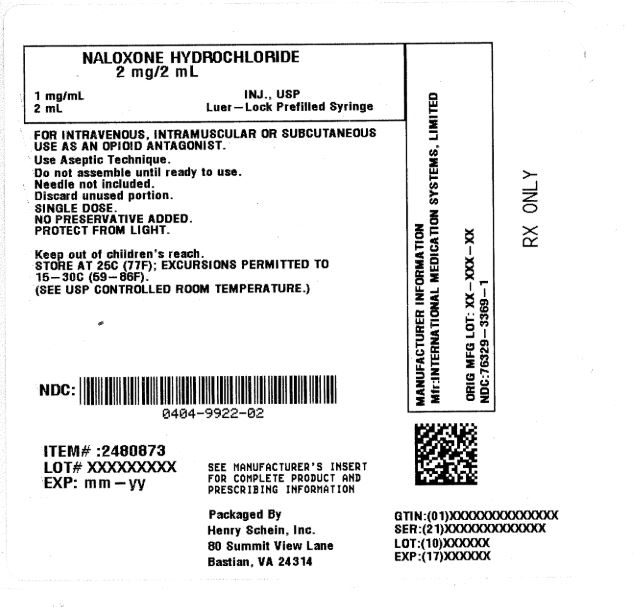 DRUG LABEL: NALOXONE HYDROCHLORIDE
NDC: 0404-9922 | Form: INJECTION
Manufacturer: Henry Schein, Inc
Category: prescription | Type: HUMAN PRESCRIPTION DRUG LABEL
Date: 20260302

ACTIVE INGREDIENTS: NALOXONE HYDROCHLORIDE 1 mg/1 mL

NALOXONE HYDROCHLORIDE INJECTION, USP
Opioid Antagonist
Rx Only

DESCRIPTION

NALOXONE HYDROCHLORIDE
INJECTION, USP
Opioid Antagonist

Rx Only

Naloxone hydrochloride, an opioid antagonist, is a synthetic congener of oxymorphone. In structure it differs from oxymorphone in that the methyl group on the nitrogen atom is replaced by an allyl group.

NALOXONE HYDROCHLORIDE
(-)-17-Allyl-4,5α-epoxy-3,14-dihydroxymorphinan-6-one hydrochloride

Naloxone hydrochloride occurs as a white to slightly off-white powder, and is soluble in water, in dilute acids, and in strong alkali; slightly soluble in alcohol; practically insoluble in ether and in chloroform.

Naloxone Hydrochloride Injection is available as a sterile solution for intravenous, intramuscular and subcutaneous administration in 1 mg/mL concentration. pH is adjusted to 3.5 ± 0.5 with hydrochloric acid. Each mL also contains 8.35 mg of sodium chloride. Naloxone Hydrochloride Injection is preservative-free.

CLINICAL PHARMACOLOGY

Complete or Partial Reversal of Opioid Depression

Naloxone hydrochloride prevents or reverses the effects of opioids including respiratory depression, sedation, and hypotension. Also, it can reverse the psychotomimetic and dysphoric effects of agonist-antagonist such as pentazocine.

Naloxone hydrochloride is an essentially pure opioid antagonist, i.e., it does not possess the “agonistic” or morphine-like properties characteristic of other opioid antagonists. When administered in usual doses and in the absence of opioids or agonistic effects of other opioid antagonists, it exhibits essentially no pharmacologic activity.

Naloxone hydrochloride has not been shown to produce tolerance or cause physical or psychological dependence. In the presence of physical dependence on opioids, naloxone hydrochloride will produce withdrawal symptoms. However, in the presence of opioid dependence, opiate withdrawal symptoms may appear within minutes of naloxone hydrochloride administration and subside in about 2 hours. The severity and duration of the withdrawal syndrome are related to the dose of naloxone hydrochloride and to the degree and type of opioid dependence.
While the mechanism of action of naloxone hydrochloride is not fully understood, in vitro evidence suggests that naloxone hydrochloride antagonizes opioid effects by competing for the μ, κ and σ opiate receptor sites in the CNS, with the greatest affinity for the μ receptor.

When naloxone hydrochloride is administered intravenously (I.V.), the onset of action is generally apparent within two minutes. The onset of action is slightly less rapid when it is administered subcutaneously (S.C.) or intramuscularly (I.M.). The duration of action is dependent upon the dose and route of administration of naloxone hydrochloride. Intramuscular administration produces a more prolonged effect than intravenous administration. Since the duration of action of naloxone hydrochloride may be shorter than that of some opiates, the effect of the opiate may return as the effects of naloxone hydrochloride dissipates. The requirement for repeat doses of naloxone hydrochloride will also be dependent upon the amount, type and route of administration of the opioid being antagonized.

Adjunctive Use in Septic Shock

Naloxone hydrochloride has been shown in some cases of septic shock to produce a rise in blood pressure that may last up to several hours; however, this pressor response has not been demonstrated to improve patient survival. In some studies, treatment with naloxone hydrochloride in the setting of septic shock has been associated with adverse effects, including agitation, nausea and vomiting, pulmonary edema, hypotension, cardiac arrhythmias, and seizures. The decision to use naloxone hydrochloride in septic shock should be exercised with caution, particularly in patients who may have underlying pain or have previously received opioid therapy and may have developed opioid tolerance.

Because of the limited number of patients who have been treated, optimal dosage and treatment regimens have not been established.

Complete or Partial Reversal of Opioid Depression

Naloxone hydrochloride prevents or reverses the effects of opioids including respiratory depression, sedation, and hypotension. Also, it can reverse the psychotomimetic and dysphoric effects of agonist-antagonist such as pentazocine.

Naloxone hydrochloride is an essentially pure opioid antagonist, i.e., it does not possess the "agonistic" or morphine-like properties characteristic of other opioid antagonists. When administered in usual doses and in the absence of opioids or agonistic effects of other opioid antagonists, it exhibits essentially no pharmacologic activity.

Naloxone hydrochloride has not been shown to produce tolerance or cause physical or psychological dependence. In the presence of physical dependence on opioids, naloxone hydrochloride will produce withdrawal symptoms. However, in the presence of opioid dependence, opiate withdrawal symptoms may appear within minutes of naloxone hydrochloride administration and subside in about 2 hours. The severity and duration of the withdrawal syndrome are related to the dose of naloxone hydrochloride and to the degree and type of opioid dependence.

While the mechanism of action of naloxone hydrochloride is not fully understood, in vitro evidence suggests that the naloxone hydrochloride antagonizes opioid effects by competing for the u, k and o opiate receptor sites in the CNS, with the greatest affinity for the u receptor.

When naloxone hydrochloride is administered intravenously (I.V.), the onset of action is generally apparent within two minutes. The onset of action is slightly less rapid when it is administered subcutaneously (S.C.) or intramuscularly (I.M.). The duration of action is dependent upon the dose and route of administration of naloxone hydrochloride. Intramuscular administration produces a more prolonged effect than intravenous administration. Since the duration of action of naloxone hydrochloride may be shorter than that of some opiates, the effect of the opiate may return as the effects of naloxone hydrochloride dissipates. The requirement for repeat doses of naloxone hydrochloride will also be dependent upon the amount, type and route of administration of the opioid being antagonized.

Adjunctive Use in Septic Shock

Naloxone hydrochloride has been shown in some cases of septic shock to produce a rise in blood pressure that may last up to several hours; however, this pressor response has not been demonstrated to improve patient survival. In some studies, treatment with naloxone hydrochloride in the setting of septic shock has been associated with adverse effects, including agitation, nausea and vomiting, pulmonary edema, hypotension, cardiac arrhythmias, and seizures. The decision to use naloxone hydrochloride in septic shock should be exercised with caution, particularly in patients who may have underlying pain or have previously received opioid therapy and may have developed opioid tolerance.

Because of the limited number of patients who have been treated, optimal dosage and treatment regimens have not been established.

PHARMACOKINETICS

Distribution

Following parenteral administration, naloxone hydrochloride is rapidly distributed in the body and readily crosses the placenta. Plasma protein binding occurs but is relatively weak. Plasma albumin is the major binding constituent but significant binding of naloxone also occurs to plasma constituents other than albumin. It is not known whether naloxone is excreted into human milk.

Metabolism and Elimination

Naloxone hydrochloride is metabolized in the liver, primarily by glucuronide conjugation with naloxone-3-glucoronide as the major metabolite. In one study the serum half-life in adults ranged from 30 to 81 minutes (mean 64 ± 12 minutes). In a neonatal study the mean plasma half-life was observed to be 3.1 ± 0.5 hours. After an oral or intravenous dose, about 25-40% of the drug is excreted as metabolites in urine within 6 hours, about 50% in 24 hours, and 60-70% in 72 hours.

Distribution

Following parenteral administration, naloxone hydrochloride is rapidly distributed in the body and readily crosses the placenta. Plasma protein binding occurs but is relatively weak. Plasma albumin is the major binding constituent but significant binding of naloxone also occurs to plasma constituents other than albumin. It is not known whether naloxone is excreted into human milk.

Metabolism and Elimination

Naloxone hydrochloride is metabolized in the liver, primarily by glucuronide conjugation with naloxone-3-glucoronide as the major metabolite. In one study the serum half-life in adults ranged from 30 to 81 minutes (mean 64 ± 12 minutes). In a neonatal study the mean plasma half-life was observed to be 3.1 ± 0.5 hours. After an oral or intravenouse dose, about 25-40% of the drug is excreted as metabolites in urine within 6 hours, about 50% in 24 hours, and 60-70% in 72 hours.

INDICATIONS AND USAGE

Naloxone hydrochloride injection is indicated for the complete or partial reversal of opioid depression, including respiratory depression, induced by natural and synthetic opioids including, propoxyphene, methadone and certain mixed agonist-antagonist analgesics: nalbuphine, pentazocine and butorphanol and cyclazocine. Naloxone hydrochloride is also indicated for the diagnosis of suspected or known acute opioid overdosage.

Naloxone hydrochloride injection may be useful as an adjunctive agent to increase blood pressure in the management of septic shock. (see CLINICAL PHARMACOLOGY; Adjunctive Use in Septic Shock).

CONTRAINDICATIONS

Naloxone hydrochloride injection is contraindicated in patients known to be hypersensitive to it or to any of the other ingredients in naloxone hydrochloride.

WARNINGS

Drug Dependence

Naloxone hydrochloride should be administered cautiously to persons including newborns of mothers who are known or suspected to be physically dependent on opioids. In such cases an abrupt and complete reversal of opioid effects may precipitate an acute withdrawal syndrome.
The signs and symptoms of opioid withdrawal in a patient physically dependent on opioids may include, but are not limited to, the following: body aches, diarrhea, tachycardia, fever, runny nose, sneezing, piloerection, sweating, yawning, nausea or vomiting, nervousness, restlessness or irritability, shivering or trembling, abdominal cramps, weakness, and increased blood pressure. In the neonate, opioid withdrawal may also include: convulsions, excessive crying, and hyperactive reflexes.

Repeat Administration

The patient who has satisfactorily responded to naloxone hydrochloride should be kept under continued surveillance and repeated doses of naloxone hydrochloride should be administered, as necessary, since the duration of action of some opioids may exceed that of naloxone hydrochloride.

Respiratory Depression due to Other Drugs

Naloxone hydrochloride is not effective against respiratory depression due to non-opioid drugs and in the management of acute toxicity caused by levopropoxyphene. Reversal of respiratory depression by partial agonists or mixed agonist/antagonists, such as buprenorphine and pentazocine, may be incomplete or require higher doses of naloxone. If an incomplete response occurs, respirations should be mechanically assisted as clinically indicated.

Drug Dependence

Naloxone hydrochloride should be administered cautiously to persons including newborns of mothers who are known or suspected to be physically dependent on opioids. In such cases an abrupt and complete reversal of opioid effects may precipitate an acute withdrawal syndrome.

The signs and symptoms of opioid withdrawal in a patient physically dependent on opioids may include, but are not limited to, the following: body aches, diarrhea, tachycardia, fever, runny nose, sneezing, piloerection, sweating, yawning, nausea or vomiting, nervousness, restlessness or irritability, shivering or trembling, abdominal cramps, weakness, and increased blood pressure. In the neonate, opioid withdrawal may also include: convulsions, excessive crying, and hyperactive reflexes.

Repeat Administration

The patient who has satisfactorily responded to naloxone hydrochloride should be kept under continued surveillance and repeated doses of naloxone hydrochloride should be administered, as necessary, since the duration of action of some opioids may exceed that of naloxone hydrochloride.

Respiratory Depression due to Other Drugs

Naloxone hydrochloride is not effective against respiratory depression due to non-opioid drugs and in the management of acute toxicity caused by levopropoxyphene. Reversal of respiratory depression by partial agonists or mixed agonist/antagonists, such as buprenorphine and pentazocine, may be incomplete or require higher doses of naloxone. If an incomplete response occurs, respirations should be mechanically assisted as clinically indicated.

PRECAUTIONS

General
In addition to naloxone hydrochloride, other resuscitative measures such as maintenance of a free airway, artificial ventilation, cardiac massage, and vasopressor agents should be available and employed when necessary to counteract acute opioid poisoning.
Abrupt postoperative reversal of opioid depression may result in nausea, vomiting, sweating, tremulousness, tachycardia, increased blood pressure, seizures, ventricular tachycardia and fibrillation, pulmonary edema, and cardiac arrest which may result in death. Excessive doses of naloxone hydrochloride in postoperative patients may result in significant reversal of analgesia and may cause agitation (see PRECAUTIONS and DOSAGE AND ADMINISTRATION; Usage in Adults-Postoperative Opioid Depression).

Several instances of hypotension, hypertension, ventricular tachycardia and fibrillation, pulmonary edema, and cardiac arrest have been reported in postoperative patients. Death, coma, and encephalopathy have been reported as sequelae of these events. These have occurred in patients most of whom had preexisting cardiovascular disorders or received other drugs which may have similar adverse cardiovascular effects. Although a direct cause and effect relationship has not been established, naloxone hydrochloride should be used with caution in patients with preexisting cardiac disease or patients who have received medications with potential adverse cardiovascular effects, such as hypotension, ventricular tachycardia or fibrillation, and pulmonary edema. It has been suggested that the pathogenesis of pulmonary edema associated with the use of naloxone hydrochloride is similar to neurogenic pulmonary edema, i.e., a centrally mediated massive catecholamine response leading to a dramatic shift of blood volume into the pulmonary vascular bed resulting in increased hydrostatic pressures.

Drug Interactions
Large doses of naloxone are required to antagonize buprenorphine since the latter has a long duration of action due to its slow rate of binding and subsequent slow dissociation from the opioid receptor. Buprenorphine antagonism is characterized by a gradual onset of the reversal effects and a decreased duration of action of the normally prolonged respiratory depression. The barbiturate methohexital appears to block the acute onset of withdrawal symptoms induced by naloxone in opiate addicts.

Carcinogenesis, Mutagenesis, Impairment of Fertility
Studies in animals to assess the carcinogenic potential of naloxone hydrochloride have not been conducted. Naloxone hydrochloride was weakly positive in the Ames mutagenicity and in the in vitro human lymphocyte chromosome aberration test but was negative in the in vitro Chinese hamster V79 cell HGPRT mutagenicity assay and in the in vivo rat bone marrow chromosome aberration study.

Reproduction studies conducted in mice and rats at doses 4-times and 8-times, respectively, the dose of a 50 kg human given 10 mg/day (when based on surface area or mg/m^2), demonstrated no embryotoxic or teratogenic effects due to naloxone hydrochloride.

Use in Pregnancy
Teratogenic Effects: Pregnancy Category C: Teratology studies conducted in mice and rats at doses 4-times and 8-times, respectively, the dose of a 50 kg human given 10 mg/day (when based on surface area or mg/m^2), demonstrated no embryotoxic or teratogenic effects due to naloxone hydrochloride. There are, however, no adequate and well-controlled studies in pregnant women. Because animal reproduction studies are not always predictive of human response, naloxone hydrochloride should be used during pregnancy only if clearly needed.

Non-teratogenic Effects: Risk-benefit must be considered before naloxone hydrochloride is administered to a pregnant woman who is known or suspected to be opioid-dependent since maternal dependence may often be accompanied by fetal dependence. Naloxone crosses the placenta, and may precipitate withdrawal in the fetus as well as in the mother. Patients with mild to moderate hypertension who receive naloxone during labor should be carefully monitored as severe hypertension may occur.

Use in Labor and Delivery
It is not known if naloxone hydrochloride affects the duration of labor and/or delivery. However, published reports indicated that administration of naloxone during labor did not adversely affect maternal or neonatal status.

Nursing Mothers: It is not known whether naloxone is excreted in human milk. Because many drugs are excreted in human milk, caution should be exercised when naloxone is administered to a nursing woman.

Pediatric Use
Naloxone hydrochloride injection, USP may be administered intravenously, intramuscularly or subcutaneously in children and neonates to reverse the effects of opiates. The American Academy of Pediatrics, however, does not endorse subcutaneous or intramuscular administration in opiate intoxication since absorption may be erratic or delayed. Although the opiate-intoxicated child responds dramatically to naloxone hydrochloride, he/she must be carefully monitored for at least 24 hours as a relapse may occur as naloxone is metabolized.

When naloxone hydrochloride is given to the mother shortly before delivery, the duration of its effect lasts only for the first two hours of neonatal life. It is preferable to administer naloxone hydrochloride directly to the neonate if needed after delivery. Naloxone hydrochloride has no apparent benefit as an additional method of resuscitation in the newly born infant with intrauterine asphyxia which is not related to opioid use.

Usage in Pediatric Patients and Neonates for Septic Shock: The safety and effectiveness of naloxone hydrochloride in the treatment of hypotension in pediatric patients and neonates with septic shock have not been established. One study of two neonates in septic shock reported a positive pressor response; however, one patient subsequently died after intractable seizures.

Geriatric Use
Clinical studies of naloxone hydrochloride did not include sufficient numbers of subjects aged 65 and over to determine whether they respond differently from younger subjects. Other reported clinical experience has not identified differences in responses between the elderly and younger patients. In general, dose selection for an elderly patient should be cautious, usually starting at the low end of the dosing range, reflecting the greater frequency of decreased hepatic, renal, or cardiac function, and of concomitant disease or other drug therapy.

Renal Insufficiency/Failure

The safety and effectiveness of naloxone hydrochloride in patients with renal insufficiency/failure have not been established in well-controlled clinical trials. Caution should be exercised when naloxone hydrochloride is administered to this patient population.

Liver Disease

The safety and effectiveness of naloxone hydrochloride in patients with liver disease have not been established in well-controlled clinical trials. Caution should be exercised when naloxone hydrochloride is administered to patients with liver disease.

ADVERSE REACTIONS

Postoperative

The following adverse events have been associated with the use of naloxone hydrochloride in postoperative patients: hypotension, hypertension, ventricular tachycardia and fibrillation, dyspnea, pulmonary edema, and cardiac arrest. Death, coma, and encephalopathy have been reported as sequelae of these events. Excessive doses of naloxone hydrochloride in postoperative patients may result in significant reversal of analgesia and may cause agitation (see PRECAUTIONS and DOSAGE AND ADMINISTRATION; Usage in Adults-Postoperative Opioid Depression).

Opioid Depression

Abrupt reversal of opioid depression may result in nausea, vomiting, sweating, tachycardia, increased blood pressure, tremulousness, seizures, ventricular tachycardia and fibrillation, pulmonary edema, and cardiac arrest which may result in death (see PRECAUTIONS).

Opioid Dependence

Abrupt reversal of opioid effects in persons who are physically dependent on opioids may precipitate an acute withdrawal syndrome which may include, but is not limited to, the following signs and symptoms: body aches, fever, sweating, runny nose, sneezing, piloerection, yawning, weakness, shivering or trembling, nervousness, restlessness or irritability, diarrhea, nausea or vomiting, abdominal cramps, increased blood pressure, tachycardia. In the neonate, opioid withdrawal may also include: convulsions; excessive crying; hyperactive reflexes (see WARNINGS).
Adverse events associated with the postoperative use of naloxone hydrochloride are listed by organ system and in decreasing order of frequency as follows:

Cardiac Disorders: pulmonary edema, cardiac arrest or failure, tachycardia, ventricular fibrillation, and ventricular tachycardia. Death, coma, and encephalopathy have been reported as sequelae of these events.
Gastrointestinal Disorders:vomiting, nausea
Nervous System Disorders: convulsions, paraesthesia, grand mal convulsion
Psychiatric Disorders: agitation, hallucination, tremulousness
Respiratory, Thoracic and Mediastinal Disorders:dyspnea, respiratory depression, hypoxia
Skin and Subcutaneous Tissue Disorders:nonspecific injection site reactions, sweating
Vascular Disorders: hypertension, hypotension, hot flushes or flushing.

See also PRECAUTIONS and DOSAGE AND ADMINISTRATION; Usage in Adults; Postoperative Opioid Depression.

Postoperative

The following adverse events have been associated with the use of naloxone hydrochloride in postoperative patients: hypotension, hypertension, ventricular tachycardia and fibrillation, dyspnea, pulmonary edema, and cardiac arrest. Death, coma, and encephalopathy have been reported as sequelae of these events. Excessive doses of naloxone hydrochloride in postoperative patients may result in significant reversal of analgesia and may cause agitation (see PRECAUTIONS and DOSAGE AND ADMINISTRATION; Usage in Adults-Postoperative Opioid Depression).

Opioid Depression

Abrupt reversal of opioid depression may result in nausea, vomiting, sweating, tachycardia, increased blood pressure, tremulousness, seizures, ventricular tachycardia and fibrillation, pulmonary edema, and cardiac arrest which may result in death (see PRECAUTIONS).

Opioid Dependence

Abrupt reversal of opioid effects in persons who are physically dependent on opioids may precipitate an acute withdrawal syndrome which may include, but is not limited to, the following signs and symptoms: body aches, fever, sweating, runny nose, sneezing, piloerection, yawning, weakness, shivering or trembling, nervousness, restlessness or irritability, diarrhea, nausea or vomiting, abdominal cramps, increased blood pressure, tachycardia. In the neonate, opioid withdrawal may also include: convulsions; excessive crying; hyperactive reflexes (see WARNINGS).

Adverse events associated with the postoperative use of naloxone hydrochloride are listed by organ system and in decreasing order of frequency as follows:

Cardiac Disorders: pulmonary edema, cardiac arrest or failure, tachycardia, ventricular fibrillation, and ventricular tachycardia. Death, coma, and encephalopathy have been reported as sequelae of these events.

Gastrointestinal Disorders: vomiting, nausea

Nervous System Disorders: convulsions, paraesthesia, grand mal convulsion

Psychiatric Disorders: agitation, hallucination, tremulousness

Respiratory, Thoracic and Mediastinal Disorders: dyspnea, respiratory depression, hypoxia

Skin and Subcutaneous Tissue Disorders: nonspecific injection site reactions, sweating

Vascular Disorders: hypertension, hypotension, hot flushes or flushing

See also PRECAUTIONS and DOSAGE AND ADMINISTRATION; Usage in Adults; Postoperative Opioid Depression.

DRUG ABUSE AND DEPENDENCE

Naloxone hydrochloride is an opioid antagonist. Physical dependence associated with the use of naloxone hydrochloride has not been reported. Tolerance to the opioid antagonist effect of naloxone hydrochloride is not known to occur.

OVERDOSAGE

There is limited clinical experience with naloxone hydrochloride overdosage in humans.

Adult Patients

In one small study, volunteers who received 24 mg/70 kg did not demonstrate toxicity. In another study, 36 patients with acute stroke received a loading dose of 4 mg/kg (10 mg/m^2/min) of naloxone hydrochloride followed immediately by 2 mg/kg/hr for 24 hours. Twenty-three patients experienced adverse events associated with naloxone use, and naloxone was discontinued in seven patients because of adverse effects. The most serious adverse events were: seizures (2 patients), severe hypertension (1), and hypotension and/or bradycardia (3).

At doses of 2 mg/kg in normal subjects, cognitive impairment and behavioral symptoms, including irritability, anxiety, tension, suspiciousness, sadness, difficulty concentrating, and lack of appetite have been reported. In addition, somatic symptoms, including dizziness, heaviness, sweating, nausea, and stomachaches were also reported. Although complete information is not available, behavioral symptoms were reported to often persist for 2-3 days.

Pediatric Patients

Up to 11 doses of 0.2 mg of naloxone (2.2 mg) have been administered to children following overdose of diphenoxylate hydrochloride with atropine sulfate. Pediatric reports include a 2-1/2 year-old child who inadvertently received a dose of 20 mg of naloxone for treatment of respiratory depression following overdose with diphenoxylate hydrochloride with atropine sulfate. The child responded well and recovered without adverse sequelae. There is also a report of a 4-1/2 year-old child who received 11 doses during a 12-hour period, with no adverse sequelae.

Patient Management

Patients who experience a naloxone hydrochloride overdose should be treated symptomatically in a closely supervised environment.

Physicians should contact a poison control center for the most up-to-date patient management information.

Adult Patients

In one small study, volunteers who received 24 mg/70 kg did not demonstrate toxicity. In another study, 36 patients with acute stroke received a loading dose of 4 mg/kg (10 mg/m2/min) of naloxone hydrochloride followed immediately by 2 mg/kg/hr for 24 hours. Twenty-three patients experienced adverse events associated with naloxone use, and naloxone was discontinued in seven patients because of adverse effects. The most serious adverse events were: seizures (2 patients), severe hypertension (1), and hypotension and/or bradycardia (3).

At doses of 2 mg/kg in normal subjects, cognitive impairment and behavioral symptoms, including irritability, anxiety, tension, suspiciousness, sadness, difficulty concentrating, and lack of appetite have been reported. In addition, somatic symptoms, including dizziness, heaviness, sweating, nausea, and stomachaches were also reported. Although complete information is not available, behavioral symptoms were reported to often persist for 2-3 days.

Pediatric Patients

Up to 11 doses of 0.2 mg of naloxone (2.2 mg) have been administered to children following overdose of diphenoxylate hydrochloride with atropine sulfate. Pediatric reports include a 2-1/2 year old child who inadvertently received a dose of 20 mg of naloxone for treatment of respiratory depression following overdose with diphenoxylate hydrochloride with atropine sulfate. The child responded well and recovered without adverse sequelae. There is also a report of a 4-1/2 year old child who received 11 doses during a 12-hour period, with no adverse sequelae.

Patient Management

Patients who experience a naloxone hydrochloride overdose should be treated symptomatically in a closely supervised environment. Physicians should contact a poison control center for the most up-to-date patient management information.

DOSAGE AND ADMINISTRATION

Naloxone hydrochloride injection may be administered intravenously, intramuscularly, or subcutaneously. The most rapid onset of action is achieved by intravenous administration, which is recommended in emergency situations.

Since the duration of action of some opioids may exceed that of naloxone, the patient should be kept under continued surveillance. Repeated doses of naloxone should be administered, as necessary.

Intravenous Infusion

Naloxone hydrochloride injection may be diluted for intravenous infusion in normal saline or 5% dextrose solutions. The addition of 2 mg of naloxone in 500 mL of either solution provides a concentration of 0.004 mg/mL. Mixtures should be used within 24 hours. After 24 hours, the remaining unused mixture must be discarded. The rate of administration should be titrated in accordance with the patient’s response.
Naloxone hydrochloride injection should not be mixed with preparations containing bisulfite, metabisulfite, long-chain or high molecular weight anions, or any solution having an alkaline pH. No drug or chemical agent should be added to naloxone hydrochloride injection unless its effect on the chemical and physical stability of the solution has first been established.

General

Parenteral drug products should be inspected visually for particulate matter and discoloration prior to administration whenever solution and container permit.

Usage in Adults

Opioid Overdose—Known or Suspected: An initial dose of 0.4 mg to 2 mg of naloxone hydrochloride may be administered intravenously. If the desired degree of counteraction and improvement in respiratory functions are not obtained, it may be repeated at two-to-three-minute intervals. If no response is observed after 10 mg of naloxone hydrochloride have been administered, the diagnosis of opioid-induced or partial opioid-induced toxicity should be questioned. Intramuscular or subcutaneous administration may be necessary if the intravenous route is not available.

Postoperative Opioid Depression: For the partial reversal of opioid depression following the use of opioids during surgery, smaller doses of naloxone hydrochloride are usually sufficient. The dose of naloxone hydrochloride should be titrated according to the patient’s response. For the initial reversal of respiratory depression, naloxone hydrochloride should be injected in increments of 0.1 to 0.2 mg intravenously at two-to three-minute intervals to the desired degree of reversal—i.e., adequate ventilationand alertness without significant pain or discomfort. Larger than necessary dosage of naloxone may result in significant reversal of analgesia and increase in blood pressure. Similarly, too rapid reversal may induce nausea, vomiting, sweating, or circulatory stress.
Repeat doses of naloxone may be required within one- to two-hour intervals depending upon the amount, type (i.e., short or long acting) and time interval since last administration of opioid. Supplemental intramuscular doses have been shown to produce a longer lasting effect.

Septic Shock:The optimal dosage of naloxone hydrochloride or duration of therapy for the treatment of hypotension in septic shock patients has not been established (see CLINICAL PHARMACOLOGY).

Usage in Children

Opioid Overdose—Known or Suspected:The usual initial dose in children is 0.01 mg/kg body weight given I.V. If this dose does not result in the desired degree of clinical improvement, a subsequent dose of 0.1 mg/kg body weight may be administered. If an l.V. route of administration is not available, naloxone may be administered I.M. or S.C. in divided doses. If necessary, naloxone hydrochloride injection can be diluted with sterile water for injection.

Postoperative Opioid Depression: Follow the recommendations and cautions under Adult Postoperative Depression. For the initial reversal of respiratory depression naloxone hydrochloride should be injected in increments of 0.005 mg to 0.01 mg intravenously at two- to three-minute intervals to the desired degree of reversal.

Usage in Neonates
Opioid-lnduced Depression: The usual initial dose is 0.01 mg/kg body weight administered I.V., I.M., or S.C. This dose may be repeated in accordance with adult administration guidelines for postoperative opioid depression.

HOW SUPPLIED

1 mg/mL naloxone hydrochloride injection USP, for intravenous, intramuscular and subcutaneous administration.

Available as follows:

1 mg/mL

2 mL single dose disposable prefilled syringes, in the MIN-I-JET® system with 21 G. x 11/2” needle. Shrink Wrapped Packages of 10.

NDC 76329-1469-1 Stock No. 1469 (contains no preservative)

2 mL single dose disposable Luer-JetTM Luer-Lock Prefilled Syringe. Shrink Wrapped Packages of 10. Needle not included.

NDC 76329-3369-1 Stock No. 3369 (contains no preservative)

Syringe Assembly Directions:

The MIN-I-JET® syringe with needle, illustrated below, is the basic unit upon which all the other syringe systems are built; slight adaptations and/ or additional auxiliary parts create the other syringe systems. Assembly directions remain essentially the same.

USE ASEPTIC TECHNIQUE

Do not assemble until ready to use.

NEEDLE NOT INCLUDED WITH STOCK NO. 3369

*CAUTION: IMPROPER ENGAGING MAY CAUSE GLASS BREAKAGE AND SUBSEQUENT INJURY.

Store at 25˚C (77˚F); excursions permitted to 15˚-30˚C (59˚-86˚F). [See USP Controlled Room Temperature.]
Protect from light.
Store in carton until contents have been used.

Repackaged by: Henry Schein, Inc., Bastian, VA 24314
From Original Manufacturer/Distributor NDC and Unit of Sale | Henry Schein Repackaged NDC and Unit of Sale | Total Strength/Total Volume (Concentration)
NDC 76329-3369-1 2 mL single dose disposable Luer-JetTM Luer-Lock Prefilled Syringe Shrink wrapped packages of 10 | NDC 0404-9922-02 1 2 mL single dose disposable Luer-JetTM Luer-Lock Prefilled Syringe in a bag (Syringe bears NDC 76329-3369-1) | 1 mg/mL

.

INTERNATIONAL MEDICATION SYSTEMS, LIMITED

SO. EL MONTE, CA 91733, U.S.A.

An Amphastar Pharmaceuticals Company

© INTERNATIONAL MEDICATION SYSTEMS, LIMITED 2023 REV.04-23